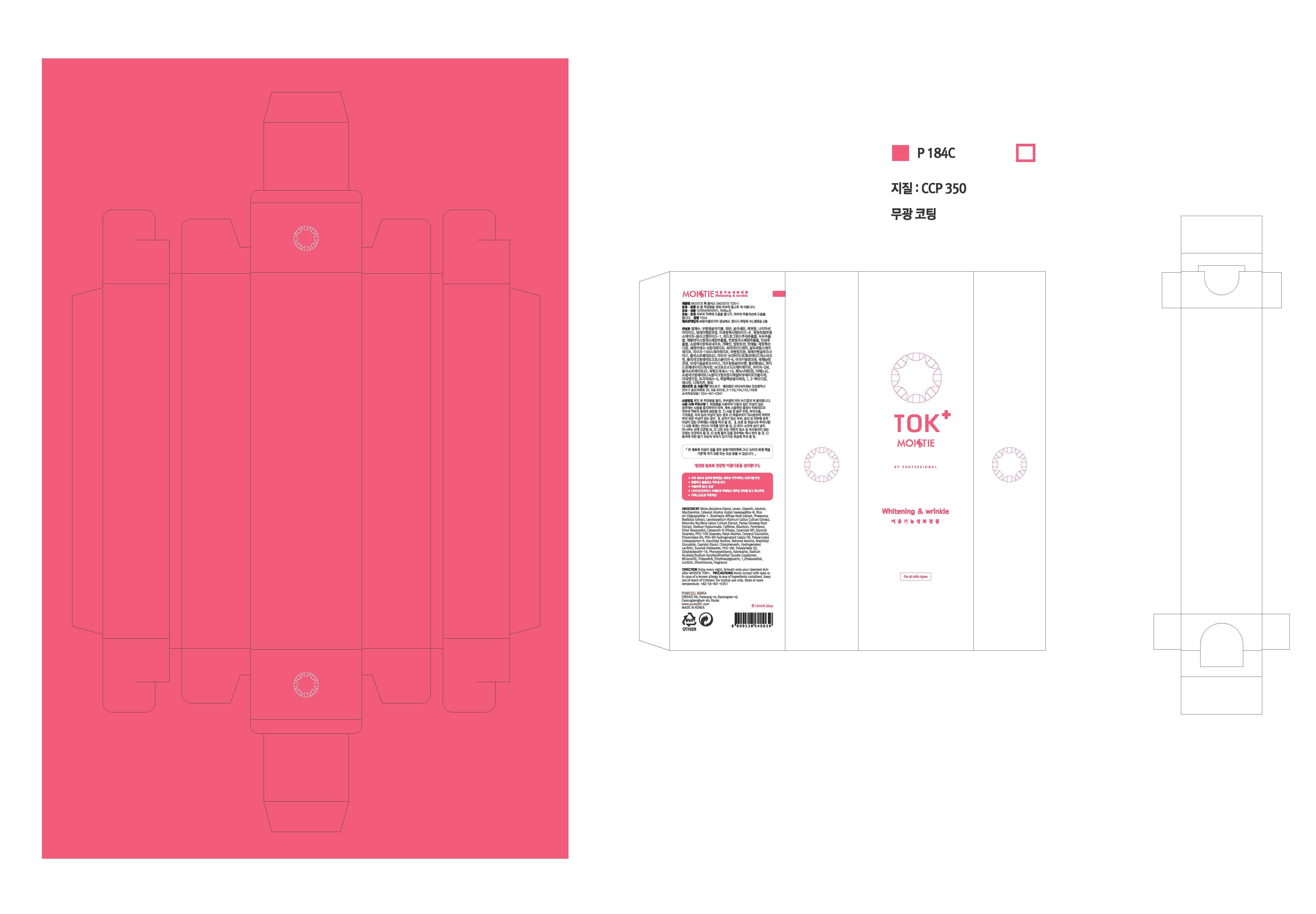 DRUG LABEL: MOISTIE TOK PLUS
NDC: 71609-0001 | Form: CREAM
Manufacturer: Purecell Korea Co., Ltd.
Category: otc | Type: HUMAN OTC DRUG LABEL
Date: 20180929

ACTIVE INGREDIENTS: NIACINAMIDE 2 g/100 mL; ADENOSINE 0.04 g/100 mL
INACTIVE INGREDIENTS: WATER; GLYCERIN; BUTYLENE GLYCOL

Drug Facts

ACTIVE INGREDIENT

Niacinamide, Adenosine

INACTIVE INGREDIENT

Water
Butylene Glycol
Levan
Glycerin
Alcohol
Acetyl Hexapeptide-8
Rice sh-Oligopeptide-1
Boerhavia diffusa Root Extract
Phaseolus Radiatus Extract
Leontopodium Alpinum Callus Culture Extract
Nelumbo Nucifera Callus Culture Extract
Panax Ginseng Root Extract
Sodium Hyaluronate
Caffeine
Allantoin
Panthenol
Ethyl Hexanediol
Ceteareth-6 Olivate
Cetearyl Alcohol
Ceramide NP
Glyceryl Stearate
PEG-100 Stearate
Batyl Alcohol
Cetearyl Glucoside
Polysorbate 60
PEG-60 Hydrogenated Castor Oil
Polyacrylate Crosspolymer-6
Arachidyl Alcohol
Behenyl Alcohol
Arachidyl Glucoside
Caprylyl Glycol
Chlorphenesin
Hydrogenated Lecithin
Sucrose Distearate
PEG-2M
Polysorbate 20
Octyldodeceth-16
Phenoxyethanol
Sodium Acrylate/Sodium Acryloyldimethyl Taurate Copolymer
Mineral Oil
Trideceth-6
Ethylhexylglycerin
1,2-Hexanediol
Lecithin
Dimethicone
Fragrance

PURPOSE

Skin Protectant - Whitening & Anti-wrinkle

keep out or reach of the children

INDICATIONS AND USAGE

After cleansing, apply your skin softner.
Apply an appropriate amount TOK PLUS along your face skin's texture.
After 10 to 20 minutes with the TOK PLUS on your face and Finish with your lotion or cream.

WARNINGS

1. Do not use in the following cases(Eczema and scalp wounds)
2.Side Effects
1)Due to the use of this druf if rash, irritation, itching and symptopms of hypersnesitivity occur dicontinue use and consult your phamacisr or doctor
3.General Precautions
1)If in contact with the eyes, wash out thoroughty with water If the symptoms are servere, seek medical advice immediately
2)This product is for exeternal use only. Do not use for internal use
4.Storage and handling precautions
1)If possible, avoid direct sunlight and store in cool and area of low humidity
2)In order to maintain the quality of the product and avoid misuse
3)Avoid placing the product near fire and store out in reach of children

DOSAGE AND ADMINISTRATION

for external use only